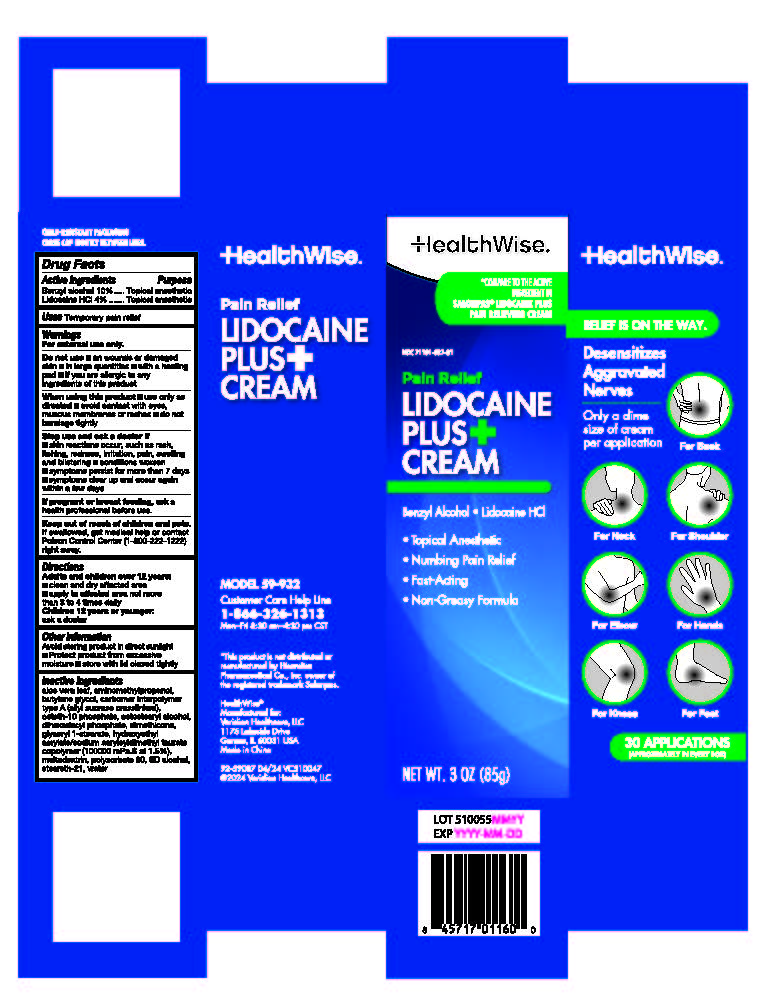 DRUG LABEL: HealthWise Lidocaine Plus Cream
NDC: 71101-037 | Form: CREAM
Manufacturer: Veridian Healthcare	
Category: otc | Type: HUMAN OTC DRUG LABEL
Date: 20240425

ACTIVE INGREDIENTS: BENZYL ALCOHOL 10 g/100 g; LIDOCAINE HYDROCHLORIDE 4 g/100 g
INACTIVE INGREDIENTS: POLYSORBATE 80; WATER; ALCOHOL; MALTODEXTRIN; HYDROXYETHYL ACRYLATE/SODIUM ACRYLOYLDIMETHYL TAURATE COPOLYMER (45000 MPA.S AT 1%); DIMETHICONE; BUTYLENE GLYCOL; DIHEXADECYL PHOSPHATE; CETOSTEARYL ALCOHOL; ALOE VERA LEAF; CETETH-10 PHOSPHATE; STEARETH-21; AMINOMETHYLPROPANOL; CARBOMER INTERPOLYMER TYPE A (55000 CPS); GLYCERYL 1-STEARATE

HealthWise Lidocaine Plus Cream

Active ingredient

Benzyl alcohol 10%

Lidocaine HCl 4%

Purpose

Topical anesthetic

Use

temporarily pain relief

Warnings

For external use only.

Do not use

- on wounds or damaged skin
- in large quantities
- with a heating pad
- if you are allergic to any ingredients of this product

When using this product

- use only as directed.
- avoid contact with eyes, mucous membranes or rashes
- do not bandage tightly

Stop use and ask a doctor if

- skin reactions occur, such as rash, itching, redness, irritation, pain, swelling and blistering
- condition worsens
- symptoms persist for more than 7 days
- symptoms clear up and occur again within a few days within a few days

If pregnant or breast-feeding,

ask a health professional before use.

Keep out of reach of children.

If swallowed, get medical help or contact a Poison Control Center (800-222-1222) right away.

Directions

adults and children over 12 years:

- clean and dry affected area
- apply a thin layer to affected area not more than 3 to 4 times daily

children 12 years or younger: ask a doctor

Inactive ingredients

Aloe Vera Leaf, Aminomethyl propanol, butylene glycol, Carbomer Interpolymer Type A (allyl sucrose crosslinked), ceteth-10 phosphate, cetostearyl alcohol, dihexadecyl phosphate, dimethicone, glyceryl 1-stearate, hydroxyethyl acrylate/sodium acryloyl dimethyl taurate copolymer (100000 mPa.S at 1.5%), maltodextrin, polysorbate 80, SD alcohol, steareth-21, water

Other information

- Avoid storing product in direct sunlight
- Protect product from excessive moisture
- Store with lid closed tightly